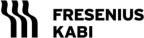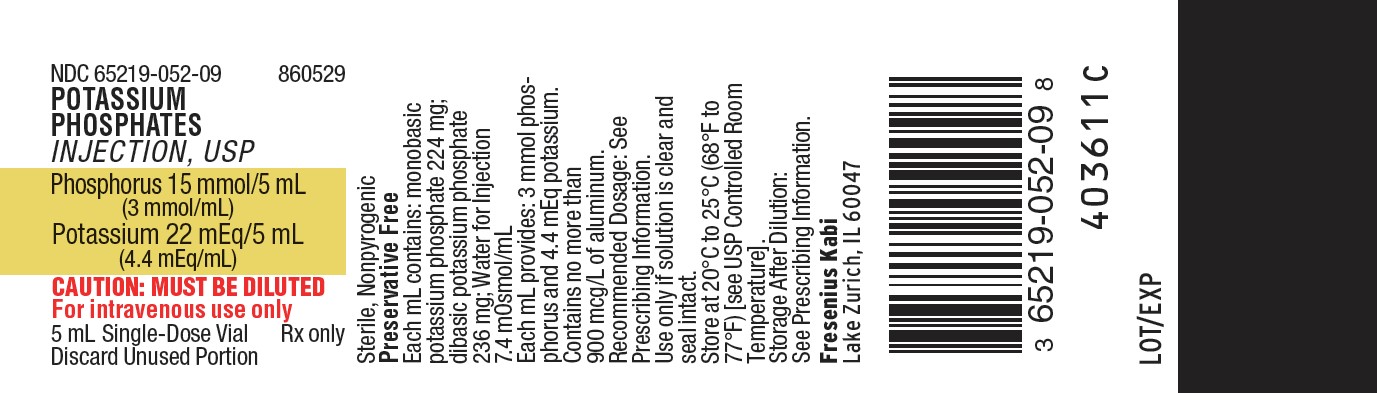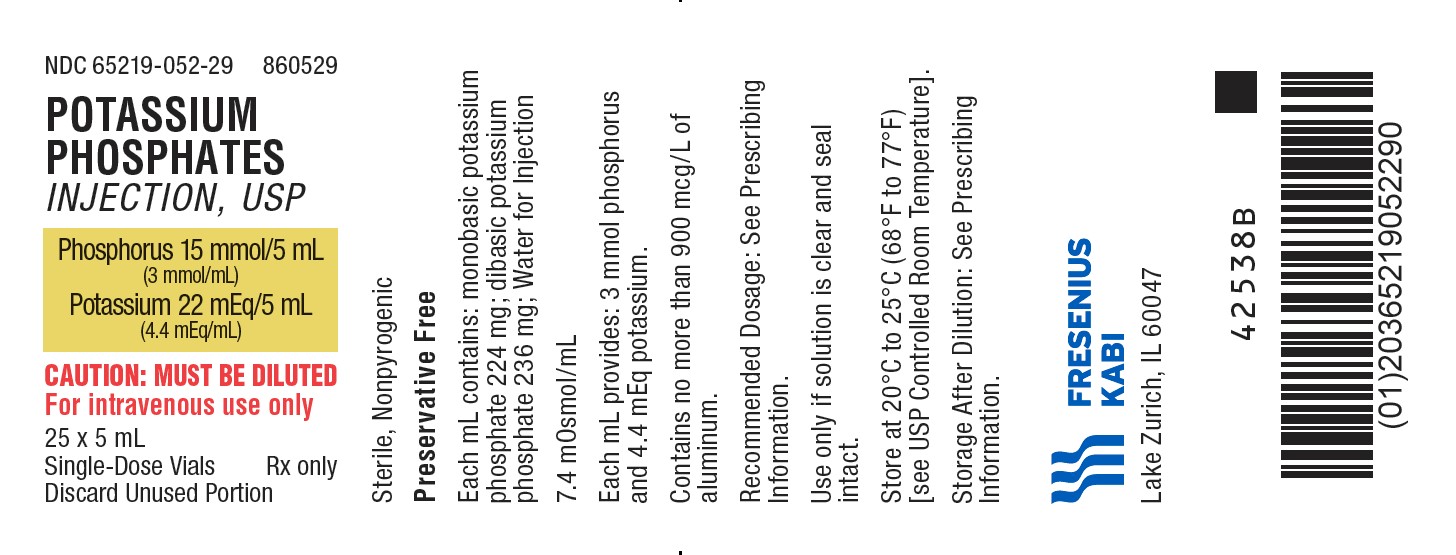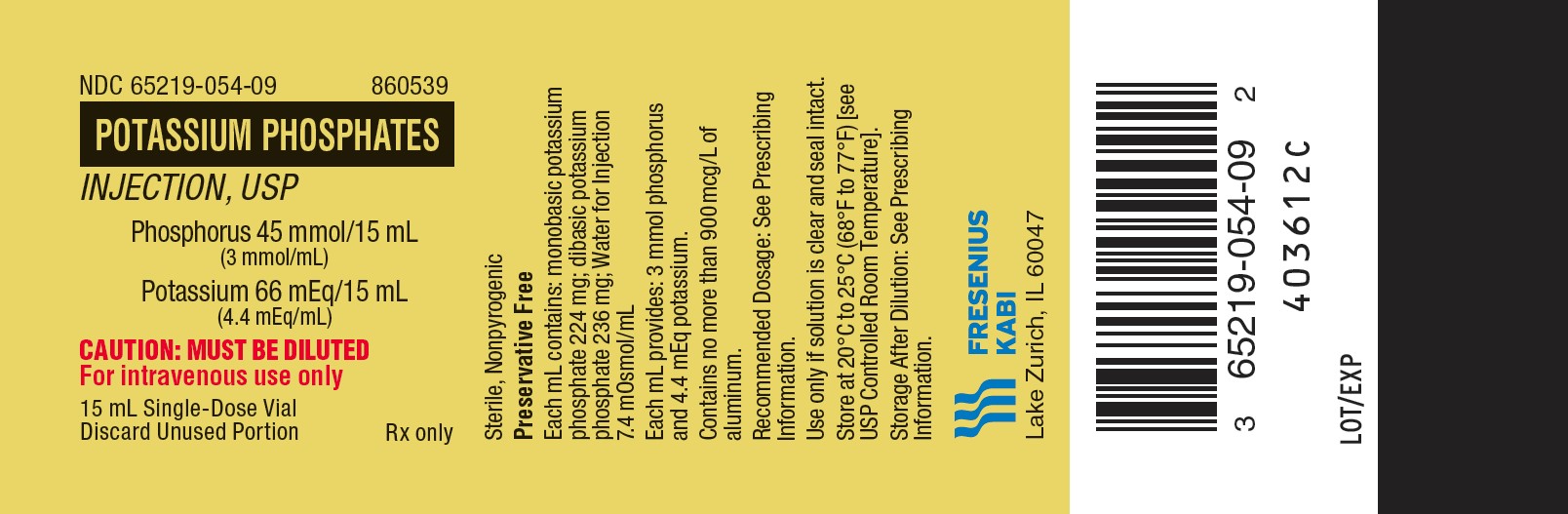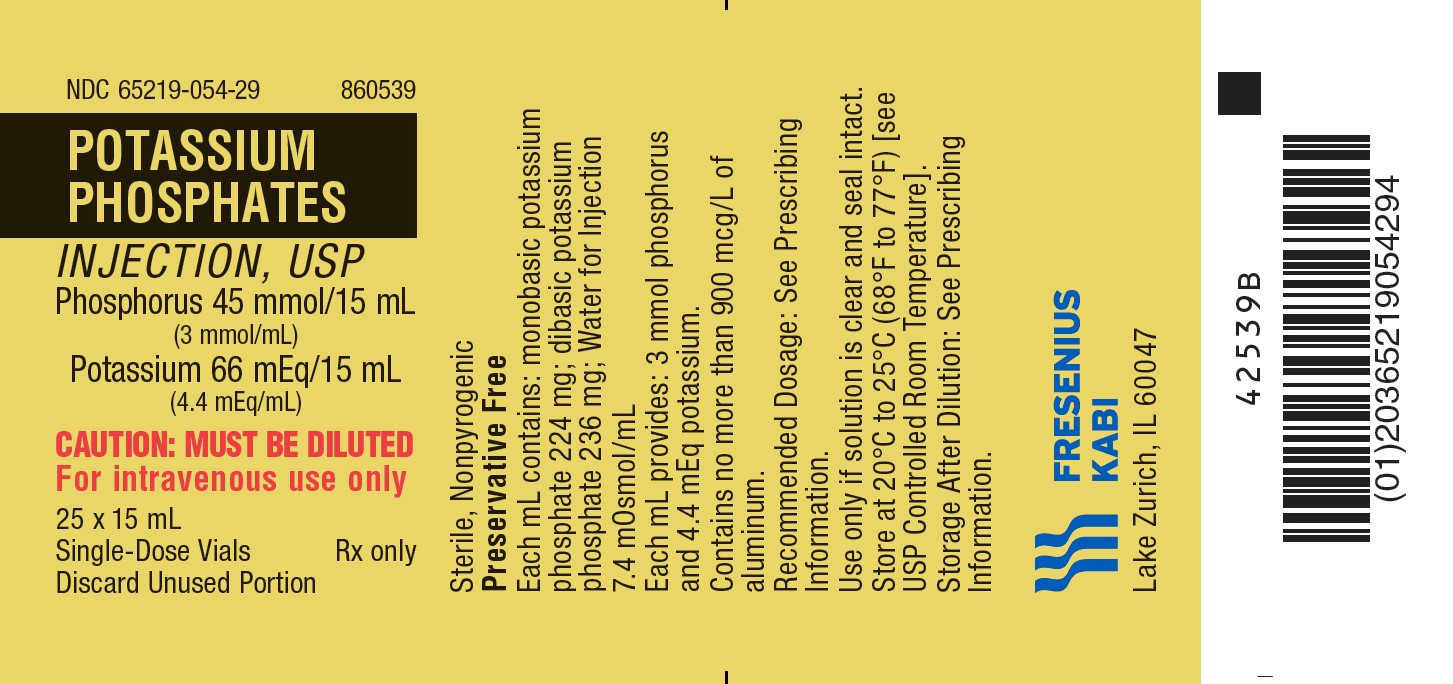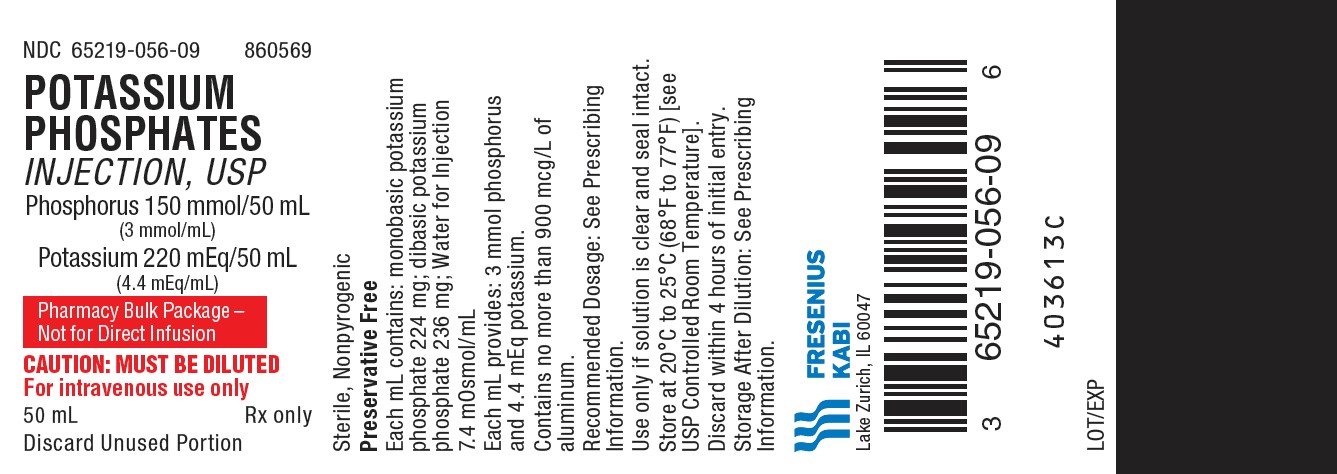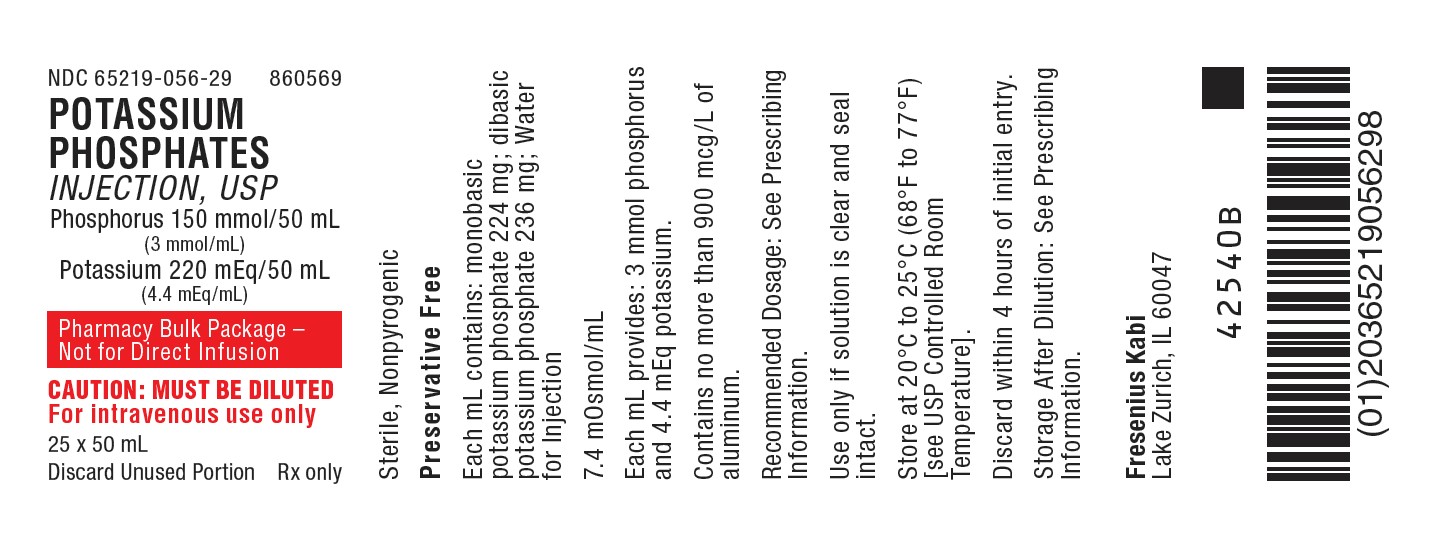 DRUG LABEL: Potassium Phosphates
NDC: 65219-052 | Form: INJECTION, SOLUTION, CONCENTRATE
Manufacturer: Fresenius Kabi USA, LLC
Category: prescription | Type: HUMAN PRESCRIPTION DRUG LABEL
Date: 20250228

ACTIVE INGREDIENTS: MONOBASIC POTASSIUM PHOSPHATE 224 mg/1 mL; DIBASIC POTASSIUM PHOSPHATE 236 mg/1 mL
INACTIVE INGREDIENTS: WATER

HIGHLIGHTS OF PRESCRIBING INFORMATION

These highlights do not include all the information needed to use POTASSIUM PHOSPHATES INJECTION safely and effectively. See full prescribing information for POTASSIUM PHOSPHATES INJECTION.
POTASSIUM PHOSPHATES injection, for intravenous use.
Initial U.S. Approval: 1983

1 INDICATIONS AND USAGE

Potassium Phosphates Injection is a phosphorus replacement product indicated as a source of phosphorus:

- in intravenous fluids to correct hypophosphatemia in adults and pediatric patients when oral or enteral replacement is not possible, insufficient or contraindicated. (1)
- for parenteral nutrition in adults and pediatric patients when oral or enteral nutrition is not possible, insufficient or contraindicated. (1)

2 DOSAGE AND ADMINISTRATION

- Administer intravenously only after dilution or admixing in a larger volume of fluid. (2.1)
- Potassium Phosphates Injection provides phosphorus 3 mmol/mL (potassium 4.4 mEq/mL). (2.2, 2.4)
- Monitor serum phosphorus, potassium, calcium, and magnesium concentrations. (2.2, 2.4)
- See full prescribing information for instructions on preparation and administration. (2.1, 2.3)

Recommended Dosage for Correction of Hypophosphatemia in Intravenous Fluids

- POTASSIUM PHOSPHATES INJECTION is only for administration to a patient with a serum potassium concentration less than 4 mEq/dL; otherwise, use an alternative source of phosphorus. (2.1)
- The dosage is dependent upon the individual needs of the patient, and the contribution of phosphorus and potassium from other sources. (2.2)
- See full prescribing information for recommendations on initial or single dosing, repeated dosing, concentration and infusion rate. (2.1, 2.2)

Recommended Dosage for Administration in Parenteral Nutrition

- Individualize the dosage based upon the patient's clinical condition, nutritional requirements, and the contribution of oral or enteral phosphorus and potassium intake. (2.4)
- See full prescribing information for recommendations for daily and maximum dosage. (2.4)

3 DOSAGE FORMS AND STRENGTHS

Injection:

- phosphorus 15 mmol/5 mL (3 mmol/mL) and potassium 22 mEq/5 mL (4.4 mEq/mL) in a single-dose vial. (3)
- phosphorus 45 mmol/15 mL (3 mmol/mL) and potassium 66 mEq/15 mL (4.4 mEq/mL) in a single-dose vial. (3)
- phosphorus 150 mmol/50 mL (3 mmol/mL) and potassium 220 mEq/50 mL (4.4 mEq/mL) as a Pharmacy Bulk Package vial.

4 CONTRAINDICATIONS

- hyperkalemia (4)
- hyperphosphatemia (4)
- hypercalcemia or significant hypocalcemia (4)
- severe renal impairment (eGFR less than 30 mL/min/1.73m^2) or end stage renal disease (4)

5 WARNINGS AND PRECAUTIONS

- Serious Cardiac Adverse Reactions with Undiluted, Bolus, or Rapid Intravenous Administration: Administer only after dilution or admixing; do not exceed the recommended infusion rate. Continuous electrocardiographic (ECG) monitoring may be needed during infusion. (2.2, 5.1)
- Pulmonary Embolism due to Pulmonary Vascular Precipitates: If signs of pulmonary distress occur, stop the infusion and initiate a medical evaluation. (5.2)
- Hyperkalemia: Increased risk in patients with renal impairment, severe adrenal insufficiency, or treated with drugs that increase potassium. Patients with cardiac disease may be more susceptible. Do not exceed the maximum daily amount of potassium or the recommended infusion rate. Continuous ECG monitoring may be needed during infusion. (5.3, 7.1)
- Hyperphosphatemia and Hypocalcemia: Monitor serum phosphorus and calcium concentrations during and following infusion. (5.4)
- Aluminum Toxicity: Increased risk in patients with renal impairment, including preterm infants. (5.5, 8.4).
- Hypomagnesemia: Reported in patients with hypercalcemia and diabetic ketoacidosis. Monitor serum magnesium concentrations during treatment. (5.6)
- Vein Damage and Thrombosis: Infuse concentrated or hypertonic solutions through a central catheter. (2.1, 2.3, 5.7)

6 ADVERSE REACTIONS

Adverse reactions include hyperkalemia, hyperphosphatemia, hypocalcemia, and hypomagnesemia. (6)

To report SUSPECTED ADVERSE REACTIONS, contact Fresenius Kabi USA, LLC at 1-800-551-7176 or FDA at 1-800-FDA-1088 or www.fda.gov/medwatch.

7 DRUG INTERACTIONS

Use of Other Medications that Increase Potassium: Avoid use in patients receiving such products. If use cannot be avoided, closely monitor serum potassium concentrations. (5.3, 7.1)

FULL PRESCRIBING INFORMATION

1 INDICATIONS AND USAGE

Potassium Phosphates Injection is indicated as a source of phosphorus:

- in intravenous fluids to correct hypophosphatemia in adults and pediatric patients when oral or enteral replacement is not possible, insufficient or contraindicated.
- for parenteral nutrition in adults and pediatric patients when oral or enteral nutrition is not possible, insufficient or contraindicated.

2 DOSAGE AND ADMINISTRATION

2.1 Preparation and Administration in Intravenous Fluids to Correct Hypophosphatemia

Preparation

- Potassium Phosphates Injection is for intravenous infusion into a central or peripheral vein only after dilution.
- Using aseptic technique, withdraw the required amount from the vial and add to 0.9% Sodium Chloride Injection, USP (normal saline) or 5% Dextrose Injection, USP (D5W). For adults and pediatric patients 12 years of age and older a total volume of 100 mL or 250 mL is recommended. For pediatric patients less than 12 years of age, use the smallest recommended volume, considering daily fluid requirements and the maximum concentration for peripheral and central administration shown in Table 1.
- The concentration of the diluted solution should take into consideration the age of the patient, the amounts of phosphorus and potassium in the dose, and is dependent upon whether administration will be through a peripheral or central venous catheter. The recommended maximum concentrations are shown in Table 1:

Table 1: Maximum Recommended Concentration of Potassium Phosphates Injection by Age and Route of Administration (Peripheral vs. Central)
Patient Population | Peripheral Venous Catheter | Central Venous Catheter
Adults and Pediatric Patients 12 Years of Age and Older | phosphorus 6.8 mmol/100 mL (potassium 10 mEq/100 mL) | phosphorus 18 mmol/100 mL (potassium 26.4 mEq/100 mL)
Pediatric Patients Less than 12 Years of Age | phosphorus 0.27 mmol/10 mL (potassium 0.4 mEq/10 mL) | phosphorus 0.55 mmol/10 mL (potassium 0.8 mEq/10 mL)

- Visually inspect the solution for particulate matter and discoloration before and after dilution and prior to administration. Do not administer unless solution is clear, and seal on the vial is intact.

Administration

- Check serum potassium and calcium concentrations prior to administration. Normalize the calcium before administering Potassium Phosphates Injection [see Contraindications (4), Warnings and Precautions (5.3, 5.4)].
- Potassium Phosphates Injection is only for administration to a patient with a serum potassium concentration less than 4 mEq/dL [see Warnings and Precautions (5.3)]. If the potassium concentration is 4 mEq/dL or more, use an alternative source of phosphorus.
- Do not infuse with calcium-containing intravenous fluids [see Warnings and Precautions (5.4)].
- The rate of administration may be dependent on the patient and the specific institution policy [see Dosage and Administration (2.2)].

Storage and Stability

- Single-Dose Vial (5 mL and 15 mL)
  - For single use only. Discard used vial, including any unused contents.
- Pharmacy Bulk Package Vial (50 mL)
  - Penetrate vial closure only one time with a suitable sterile transfer device or dispensing set that allows measured dispensing of the contents.
  - Use Potassium Phosphates Injection promptly once the sterile transfer set has been inserted into the Pharmacy Bulk Package vial or a maximum of 4 hours at room temperature 20°C to 25°C (68°F to 77°F) (25°C to 77°F) after the container closure has been penetrated. Discard any remaining drug.
- After dilution, the solution is stable for a maximum of 4 hours at room temperature 20°C to 25°C (68°F to 77°F) or 14 days under refrigeration at 2°C to 8°C (36°F to 46°F).

2.2 Dosage for Administration in Intravenous Fluids to Correct Hypophosphatemia

Potassium Phosphates Injection provides phosphorus 3 mmol/mL (potassium 4.4 mEq/mL).

The dosage is dependent upon the individual needs of the patient, and the contribution of phosphorus and potassium from other sources.

Initial or Single Dose

The phosphorus doses in Table 2 are general recommendations for an initial or single dose and are intended for most patients. Based upon clinical requirements, some patients may require a lower or higher dose. The maximum initial or single dose of phosphorus is 45 mmol (potassium 66 mEq) [see Warnings and Precautions (5.1)].

In patients with moderate renal impairment (eGFR ≥30 mL/min/1.73 m^2 to <60 mL/min/1.73 m^2), start at the low end of the dose range [see Use in Specific Populations (8.6)].

Monitor serum phosphorus, potassium, calcium and magnesium serum concentrations.

Table 2: Recommended Initial or Single Dose of Potassium Phosphates Injection in Intravenous Fluids to Correct Hypophosphatemia in Adults and Pediatric Patients
Serum Phosphorus Concentrationa | Phosphorus Dosageb,c | Corresponding Potassium Content
1.8 mg/dL to lower end of the reference rangea | 0.16 mmol/kg to 0.31 mmol/kg | potassium; 0.23 mEq/kg to 0.46 mEq/kg
1 mg/dL to 1.7 mg/dL | 0.32 mmol/kg to 0.43 mmol/kg | potassium; 0.47 mEq/kg to 0.63 mEq/kg
Less than 1 mg/dL | 0.44 mmol/kg to 0.64 mmol/kgc | potassium; 0.64 mEq/kg to 0.94 mEq/kg
a Serum phosphorus reported using 2.5 mg/dL as the lower end of the reference range for healthy adults and pediatric patients 12 months of age and older. Serum phosphorus reported using 4 mg/dL as the lower end of the reference range for preterm and term infants less than 12 months of age. Serum phosphorus concentrations may vary depending on the assay used and the laboratory reference range.
b Weight is in terms of actual body weight. Limited information is available regarding dosing of patients significantly above ideal body weight; consider using an adjusted body weight for these patients.
c up to a maximum of phosphorus 45 mmol (potassium 66 mEq) as a single dose.

Concentration and Intravenous Infusion Rate

- The concentration of the diluted solution [see Table 1, Dosage and Administration (2.1)] and the infusion rate is dependent upon whether administration will be through a peripheral or central venous catheter. The maximum recommended infusion rates are shown in Table 3 for adults and pediatric patients 12 years of age and older.

Table 3: Maximum Recommended Infusion Rate of Potassium Phosphates Injection for Adults and Pediatric Patients 12 Years of Age and Older
Route of Administration | Maximum Infusion Rate
Peripheral Venous Catheter | phosphorus 6.8 mmol/hour (potassium 10 mEq/hour)
Central Venous Catheter | phosphorus 15 mmol/hour (potassium 22 mEq/hour)

Continuous electrocardiographic (ECG) monitoring and infusion through a central venous catheter is recommended for infusion rates higher than:

- Potassium 10 mEq/hour for adults and pediatric patients weighing 20 kg or greater
- Potassium 0.5 mEq/kg/hour for pediatric patients weighing less than 20 kg

Repeated Dosing

Additional dose(s) following the initial dose may be needed in some patients. Prior to administration of additional doses, assess the patient clinically, obtain serum phosphorus, calcium and potassium concentrations and adjust the dose accordingly.

2.3 Preparation and Administration in Parenteral Nutrition

- Potassium Phosphates Injection is for intravenous infusion into a peripheral or central vein only after dilution and admixing.
- Potassium Phosphates Injection is to be prepared only in a suitable work area such as a laminar flow hood (or an equivalent clean air compounding area). The key factor in the preparation is careful aseptic technique to avoid inadvertent touch contamination during mixing of solutions and addition of other nutrients.
- Transfer the required amount of Potassium Phosphates Injection to the parenteral nutrition solution following the admixture of amino acids, dextrose, electrolytes solutions, and prior to lipids (if added).
- Because additives may be incompatible, evaluate all additions to the parenteral nutrition container for compatibility and stability of the resulting preparation.
- Calcium and phosphate ratios must be considered. Excess addition of calcium and phosphate, especially in the form of mineral salts, may result in the formation of calcium-phosphate precipitates [see Warnings and Precautions (5.2)]. Calcium-phosphate stability in parenteral nutrition solutions is dependent upon the pH of the solution, temperature, and relative concentration of each ion. Discard if any precipitates are observed.
- Inspect the final parenteral solution containing Potassium Phosphates Injection to ensure that:
  - precipitates have not formed during mixing or addition of additives and inspect again before administration.
  - the emulsion has not separated, if lipids have been added. Separation of the emulsion can be visibly identified by a yellowish streaking or the accumulation of yellowish droplets in the admixed emulsion.
- The final parenteral nutrition solution is for intravenous infusion into a peripheral or central vein. The choice of a peripheral or central venous route should depend on the osmolarity of the final infusate. Solutions with osmolarity of 900 mOsmol/L or greater must be infused through a central catheter [see Warnings and Precautions (5.7)].

Storage

- Protect the parenteral nutrition solution from light during storage.

Stability

- Single-Dose Vial (5 mL and 15 mL)
  - For single use only. Discard used vial, including any unused contents.
- Pharmacy Bulk Package Vial (50 mL)
  - Penetrate vial closure only one time with a suitable sterile transfer device or dispensing set that allows measured dispensing of the contents.
  - Use Potassium Phosphates Injection for admixing promptly once the sterile transfer set has been inserted into the Pharmacy Bulk Package vial or a maximum of 4 hours at room temperature 20°C to 25°C (68°F to 77°F) (25ºC to 77ºF) after the container closure has been penetrated. Discard any remaining drug.
  - Use parenteral nutrition solution containing Potassium Phosphates Injection promptly after mixing. Any storage of the admixture should be under refrigeration from 2°C to 8°C (36°F to 46°F) and limited to a brief period of time, no longer than 24 hours. After removal from refrigeration, bring to room temperature and use promptly and complete the infusion within 24 hours. Discard any remaining admixture.

2.4 Dosage for Administration in Parenteral Nutrition

Potassium Phosphates Injection provides phosphorus 3 mmol/mL (potassium 4.4 mEq/mL).

The recommended daily dosage in parenteral nutrition is shown in Table 4. Individualize the dosage based upon the patient's clinical condition, nutritional requirements, and the contribution of oral or enteral phosphorus and potassium intake. The amount of phosphorus that can be added to parenteral nutrition may be limited by the amount of calcium that is also added to the solution.

Table 4: Recommended Daily Dosage of Potassium Phosphates Injection for Parenteral Nutrition for Adults and Pediatric Patients
Patient Population | Generally Recommended Phosphorus Daily Dosage; (Potassium Content)
Preterm and Term Infants Less than 12 Months | 2 mmol/kg/day; (potassium 2.9 mEq/kg/day)
Pediatric Patients 1 year to Less Than 12 years | 1 mmol/kg/day; up to 40 mmol/day; (potassium 1.5 mEq/kg/day; up to 58.7 mEq/day)
Adults and Pediatric Patients 12 Years of Age and Older | 20 mmol/day to 40 mmol/daya; (potassium 29.3 mEq/day to 58.7 mEq/day)
a In patients with moderate renal impairment (eGFR ≥30 mL/min/1.73 m^2 to <60 mL/min/1.73 m^2), start at the low end of the dosage range

Monitoring

Monitor serum phosphorus, potassium, calcium and magnesium concentrations and adjust the dosage accordingly.

3 DOSAGE FORMS AND STRENGTHS

Potassium Phosphates Injection, USP is a clear and colorless solution supplied as:

- phosphorus 15 mmol/5 mL (3 mmol/mL) and potassium 22 mEq/5 mL (4.4 mEq /mL) in a single-dose vial.
- phosphorus 45 mmol/15 mL (3 mmol/mL) and potassium 66 mEq/15 mL (4.4 mEq/mL) in a single-dose vial.
- phosphorus 150 mmol/50 mL (3 mmol/mL) and potassium 220 mEq/50 mL (4.4 mEq/mL) in Pharmacy Bulk Package vial.

4 CONTRAINDICATIONS

Potassium Phosphates Injection is contraindicated in patients with:

- hyperkalemia [see Warning and Precautions (5.3)]
- severe renal impairment (eGFR less than 30 mL/min/1.73m^2) or end stage renal disease [see Warning and Precautions (5.3)]
- hyperphosphatemia [see Warning and Precautions (5.4)]
- hypercalcemia or significant hypocalcemia [see Warning and Precautions (5.4)]

5 WARNINGS AND PRECAUTIONS

5.1 Serious Cardiac Adverse Reactions with Undiluted, Bolus or Rapid Intravenous Administration

Intravenous administration of potassium phosphates to correct hypophosphatemia in single doses of phosphorus 50 mmol and greater and/or at rapid infusion rates (over 1 to 3 hours) in intravenous fluids has resulted in death, cardiac arrest, cardiac arrhythmia (including QT prolongation), hyperkalemia, hyperphosphatemia, and seizures [see Overdosage (10)]. In addition, inappropriate intravenous administration of undiluted or insufficiently diluted potassium phosphates as a rapid “IV push” has resulted in cardiac arrest, cardiac arrhythmias, hypotension, and death.

Potassium Phosphates Injection is for intravenous infusion only after dilution or admixing. The maximum initial or single dose of Potassium Phosphates Injection in intravenous fluids to correct hypophosphatemia is phosphorus 45 mmol (potassium 66 mEq). The recommended infusion rate for administration through a peripheral venous catheter is approximately phosphorus 6.8 mmol/hour (potassium 10 mEq/hour). Continuous electrocardiographic (ECG) monitoring is recommended for higher infusion rates [see Dosage and Administration (2.1, 2.2)].

5.2 Pulmonary Embolism due to Pulmonary Vascular Precipitates

Pulmonary vascular emboli and pulmonary distress related to precipitates in the pulmonary vasculature have been described in patients receiving admixed products containing calcium and phosphate or parenteral nutrition. The cause of precipitate formation has not been determined in all cases; however, in some fatal cases, pulmonary emboli occurred as a result of calcium phosphate precipitates. Precipitation has occurred following passage through an in-line filter; in vivo precipitate formation may also have occurred. If signs of pulmonary distress occur, stop the parenteral nutrition infusion and initiate a medical evaluation. In addition to inspection of the solution [see Dosage and Administration (2.3)], the infusion set and catheter should also periodically be checked for precipitates.

5.3 Hyperkalemia

Potassium Phosphates Injection may increase the risk of hyperkalemia, including life-threatening cardiac events, especially when administered in excessive doses, undiluted or by rapid intravenous infusion [see Warnings and Precautions (5.1)]. Patients with severe renal impairment and end stage renal disease are at increased risk of developing life-threatening hyperkalemia, when administered intravenous potassium [see Contraindications (4)]. Other patients at increased risk of hyperkalemia include those with severe adrenal insufficiency or treated concurrently with other drugs that cause or increase the risk of hyperkalemia [see Drug Interactions (7.1)]. Patients with cardiac disease may be more susceptible to the effects of hyperkalemia.

Consider the amount of potassium from all sources when determining the dose of Potassium Phosphates Injection and do not exceed the maximum age- appropriate recommended daily amount of potassium. In patients with moderate renal impairment (eGFR ≥30 mL/min/1.73 m^2 to <60 mL/min/1.73 m^2), start at the low end of the dose range and monitor serum potassium, phosphorus, calcium, and magnesium concentrations [see Dosage and Administration (2.2, 2.4), Use in Specific Populations (8.6)].

When administering Potassium Phosphates Injection in intravenous fluids to correct hypophosphatemia, check the serum potassium concentration prior to administration. If the potassium concentration is 4 mEq/dL or more, do not administer Potassium Phosphates Injection and use an alternative source of phosphorus [see Dosage and Administration (2.1)].

The maximum initial or single dose of Potassium Phosphates Injection in intravenous fluids to correct hypophosphatemia is phosphorus 45 mmol (potassium 66 mEq). The recommended infusion rate of potassium through a peripheral venous catheter is 10 mEq/hour. Continuous electrocardiographic (ECG) monitoring is recommended for higher infusion rates of potassium [see Dosage and Administration (2.2)].

5.4 Hyperphosphatemia and Hypocalcemia

Hyperphosphatemia can occur with intravenous administration of potassium phosphates, especially in patients with renal impairment. Hyperphosphatemia can cause the formation of insoluble calcium phosphorus products with consequent hypocalcemia, neurological irritability with tetany, nephrocalcinosis with acute kidney injury and more rarely, cardiac irritability with arrhythmias.

Obtain serum calcium concentrations prior to administration and normalize the calcium before administering Potassium Phosphates Injection. Potassium Phosphates Injection is contraindicated in patients with hyperphosphatemia and/or hypercalcemia [see Contraindications (4)].

Monitor serum phosphorus and calcium concentrations during treatment with Potassium Phosphates Injection [see Dosage and Administration (2.2, 2.4)].

5.5 Aluminum Toxicity

Potassium Phosphates Injection contains aluminum that may be toxic.

Aluminum may reach toxic levels with prolonged parenteral administration in patients with renal impairment. Preterm infants are particularly at risk for aluminum toxicity because their kidneys are immature, and they require large amounts of calcium and phosphate containing solutions, which also contain aluminum.

Patients with renal impairment, including preterm infants, who receive greater than 4 to 5 mcg/kg/day of parenteral aluminum can accumulate aluminum at levels associated with central nervous system and bone toxicity. Tissue loading may occur at even lower rates of administration.

Exposure to aluminum from Potassium Phosphates Injection is no more than 0.6 mcg/kg/day when patients are administered the recommended dosage [see Dosage and Administration (2.4), Description (11)].

When prescribing Potassium Phosphates Injection for use in parenteral nutrition solutions containing other small volume parenteral products, the total daily patient exposure to aluminum from the admixture should be considered and maintained at no more than 5 mcg/kg/day [see Use in Specific Populations (8.4)].

5.6 Hypomagnesemia

Intravenous infusion of phosphate has been reported to cause a decrease in serum magnesium (and calcium) concentrations when administered to patients with hypercalcemia and diabetic ketoacidosis. Monitor serum magnesium concentrations during treatment.

5.7 Vein Damage and Thrombosis

Potassium Phosphates Injection must be diluted and administered in intravenous fluids or used as an admixture in parenteral nutrition. It is not for direct intravenous infusion. The infusion of hypertonic solutions into a peripheral vein may result in vein irritation, vein damage, and/or thrombosis. The primary complication of peripheral administration is venous thrombophlebitis, which manifests as pain, erythema, tenderness or a palpable cord. Remove the catheter as soon as possible and initiate appropriate medical treatment if thrombophlebitis develops.

When administered peripherally in intravenous fluids to correct hypophosphatemia, a generally recommended maximum concentration is phosphorus 6.8 mmol/100 mL (potassium 10 mEq/100 mL) [see Dosage and Administration (2.1)]

Parenteral nutrition solutions with an osmolarity of 900 mOsmol/L or greater must be infused through a central catheter [see Dosage and Administration (2.3)].

5.8 Laboratory Monitoring

Monitor serum phosphorus, potassium, calcium and magnesium concentrations during treatment [see Dosage and Administration (2.2, 2.4)].

6 ADVERSE REACTIONS

The following clinically significant adverse reactions are described elsewhere in the labeling:

- Aluminum Toxicity [see Warnings and Precautions (5.5)]
- Hypomagnesemia [see Warnings and Precautions (5.6)]
- Vein Damage and Thrombosis [see Warnings and Precautions (5.7)]

The following adverse reactions in Table 5 have been reported in clinical studies or postmarketing reports in patients receiving intravenously administered potassium phosphates. Because some of these reactions were reported voluntarily from a population of uncertain size, it is not always possible to reliably estimate their frequency or establish a causal relationship to drug exposure.

Table 5: Adverse Reactions Reported in Clinical Studies or Postmarketing Reports with Intravenous Potassium Phosphates
System Organ Class | Adverse Reactions
Metabolism and Nutrition Disorders | pulmonary embolism due to pulmonary vascular precipitates [see Warnings and Precautions (5.2)], hyperkalemia [see Warnings and Precautions (5.3)], hyperphosphatemia [see Warnings and Precautions (5.4)], hypocalcemia [see Warnings and Precautions (5.5)], hypovolemia, and osmotic diuresis
Cardiac Disorders | hypotension, arrhythmia, heart block, cardiac arrest, bradycardia, chest pain, ECG changes [see Warnings and Precautions (5.1)], and edema
Respiratory, Thoracic, and Mediastinal Disorders | dyspnea [see Warnings and Precautions (5.2)]
Renal and Urinary Disorders | acute phosphate nephropathy (i.e., nephrocalcinosis with acute kidney injury), decreased urine output, and transition to chronic kidney disease [see Warnings and Precautions (5.4)]
Gastrointestinal Disorders | diarrhea, stomach pain
Musculoskeletal and Connective Tissue Disorders | weakness
Nervous System Disorders | confusion, lethargy, paralysis, paresthesia

7 DRUG INTERACTIONS

7.1 Other Products that Increase Serum Potassium

Administration of Potassium Phosphates Injection to patients treated concurrently or recently with products that increase serum potassium (e.g., potassium- sparing diuretics, ACE inhibitors, angiotensin II receptor antagonists, digoxin, or the immunosuppressants tacrolimus and cyclosporine) increases the risk of severe and potentially fatal hyperkalemia, in particular in the presence of other risk factors for hyperkalemia [see Warnings and Precautions (5.3)]. Avoid use of Potassium Phosphates Injection in patients receiving such products. If use cannot be avoided, closely monitor serum potassium concentrations [see Dosage and Administration (2.2, 2.4)].

8 USES IN SPECIFIC POPULATIONS

8.1 Pregnancy

Risk Summary

Administration of the recommended dose of Potassium Phosphates Injection is not expected to cause major birth defects, miscarriage, or adverse maternal or fetal outcomes. Animal reproduction studies have not been conducted with Potassium Phosphates Injection.

The estimated background risk of major birth defects and miscarriage for the indicated population is unknown. All pregnancies have a background risk of birth defect, loss, or other adverse outcomes. In the U.S. general population, the estimated background risk of major birth defects and miscarriage in clinically recognized pregnancies is 2 to 4% and 15 to 20%, respectively.

Clinical Considerations

Disease-associated Maternal and/or Embryo-Fetal Risk

Phosphorus is an essential mineral element. Parenteral supplementation with potassium phosphates should be considered if a pregnant woman's requirements cannot be fulfilled by oral or enteral intake.

8.2 Lactation

Risk Summary

Phosphorus and potassium are present in human milk. Administration of the recommended dose of Potassium Phosphates Injection is not expected to cause harm to a breastfed infant. There is no information on the effects of potassium phosphates on milk production. The development and health benefits of breastfeeding should be considered along with the mother's clinical need for Potassium Phosphates Injection and any potential adverse effects on the breastfed child from Potassium Phosphates Injection or from underlying maternal condition.

8.4 Pediatric Use

Safety and effectiveness of Potassium Phosphates Injection have been established in pediatric patients as a source of phosphorus:

- in intravenous fluids to correct hypophosphatemia when oral or enteral replacement is not possible, insufficient, or contraindicated.
- for parenteral nutrition when oral or enteral nutrition is not possible, insufficient, or contraindicated.

Because of immature renal function, preterm infants receiving prolonged parenteral nutrition treatment with Potassium Phosphates Injection may be at higher risk of aluminum toxicity. [see Warnings and Precautions (5.5)].

8.5 Geriatric Use

In general, dose selection of Potassium Phosphates Injection for an elderly patient should be cautious, starting at the low end of the dosing range because of the greater frequency of decreased hepatic, renal, or cardiac function, and of concomitant disease or other drug therapy. It may be useful to monitor renal function during treatment [see Use in Specific Populations (8.6)].

8.6 Renal Impairment

Potassium and phosphorus are known to be substantially excreted by the kidney and the risk of adverse reactions to Potassium Phosphates Injection may be greater in patients with impaired renal function [see Warnings and Precautions (5.3, 5.4, 5.5)].

Potassium Phosphates Injection is contraindicated due to the risk of hyperkalemia in patients with severe renal impairment (eGFR less than 30 mL/min/1.73 m^2) or end stage renal disease [see Contraindications (4)].

In patients with moderate renal impairment (eGFR ≥ 30 mL/min/1.73 m^2 to < 60 mL/min/1.73 m^2), start at the low end of the dosage range and monitor serum potassium, phosphorus, calcium, and magnesium concentrations [see Dosage and Administration (2.2, 2.4)].

10 OVERDOSAGE

Hyperphosphatemia

Administration of excessive doses of intravenous potassium phosphates in intravenous fluids as a single dose ranging from approximately 50 to 270 mmol phosphorus and/or at rapid infusion rates (over 1 to 3 hours) has resulted in death, cardiac arrest, cardiac arrhythmia (including QT prolongation), hyperkalemia, hyperphosphatemia, seizures, and tetany.

Hyperphosphatemia is particularly a risk in patients with renal failure. Hyperphosphatemia leads in turn to hypocalcemia, which may be severe, and to ectopic calcification, particularly in patients with initial hypercalcemia. Tissue calcification may cause hypotension and organ damage and result in acute renal failure.

Hyperkalemia

Excessive administration of phosphates given as potassium salts may also cause hyperkalemia. Manifestations of hyperkalemia include:

- Disturbances in cardiac conduction and arrhythmias, including bradycardia, heart block, asystole, ventricular tachycardia, ventricular fibrillation
- Hypotension
- Muscle weakness including paresthesia, muscular and respiratory paralysis

Management

In the event of overdosage, discontinue infusions containing potassium phosphates immediately and institute general supportive measures, including ECG monitoring, laboratory monitoring, and correction of serum electrolyte concentrations, especially potassium, phosphorus, calcium, and magnesium.

11 DESCRIPTION

Potassium Phosphates Injection, USP, a phosphorus replacement product containing phosphorus 3 mmol/mL and potassium 4.4 mEq/mL. It is a sterile, non-pyrogenic, concentrated solution containing a mixture of monobasic potassium phosphate and dibasic potassium phosphate in water for injection. It is supplied as a 5 mL and 15 mL single-dose vials and a 50 mL Pharmacy Bulk Package vial.

Monobasic Potassium Phosphate is chemically designated KH2PO4, molecular weight 136.09, white, odorless crystals or granules freely soluble in water.

Dibasic Potassium Phosphate is chemically designated K2HPO4, molecular weight 174.18, colorless or white granular salt freely soluble in water.

Each mL contains 224 mg of monobasic potassium phosphate and 236 mg of dibasic potassium phosphate.

Each mL contains 3 mmol phosphorus (equivalent to 93 mg phosphorus) and 4.4 mEq potassium (equivalent to 170 mg of potassium). Note: 1 mmol of phosphorus is equal to 1 mmol phosphate. The pH is 6.0 to 7.0.

This product contains no more than 900 mcg/L of aluminum [see Warnings and Precautions (5.5)].

The osmolarity is 7.4 mOsmol/mL (calc).

The solution is administered after dilution or admixing by the intravenous route.

12 CLINICAL PHARMACOLOGY

12.1 Mechanism of Action

Phosphorus in the form of organic and inorganic phosphate has a variety of biochemical functions in all organs and tissues, including critical roles in nucleic acid structure, energy storage and transfer, cell signaling, cell membrane composition and structure, acid-base balance, mineral homeostasis and bone mineralization.

12.3 Pharmacokinetics

Distribution

Approximately 85% of serum phosphates is free and ultra-filterable and 15% is protein-bound.

Elimination

Intravenously infused phosphates not taken up by the tissues are excreted almost entirely in the urine. Serum phosphorus is believed to be filterable by the renal glomeruli and the major portion of filtered phosphorus (greater than 80%) is actively reabsorbed by the tubules.

16 HOW SUPPLIED/STORAGE AND HANDLING

Potassium Phosphates Injection, USP is a clear and colorless solution supplied as phosphorus 3 mmol/mL and potassium 4.4 mEq/mL as shown:

Product Code | Unit of Sale | Strength | Each
860529 | NDC 65219-052-29; Tray containing 25 units | Phosphorus 15 mmol/5 mL and; Potassium 22 mEq/5 mL | NDC 65219-052-09; 5 mL single dose, plastic vial
860539 | NDC 65219-054-29; Tray containing 25 units | Phosphorus 45 mmol/15 mL and; Potassium 66 mEq/15 mL | NDC 65219-054-09; 15 mL single dose, plastic vial
860569 | NDC 65219-056-29; Tray containing 25 units | Phosphorus 150 mmol/50 mL and; Potassium 220 mEq/50 mL | NDC 65219-056-09; 50 mL fill Pharmacy Bulk Package, plastic vial.

Store at 20°C to 25°C (68°F to 77°F) [see USP Controlled Room Temperature].

Pharmacy Bulk Package vial: Discard within 4 hours of initial entry [see Dosage and Administration (2.3)].

For storage of admixed solution see Dosage and Administration 2.1, 2.3.

17 PATIENT COUNSELING INFORMATION

Inform patients, caregivers or home healthcare providers of the following risks of Potassium Phosphates Injection:

- Serious Cardiac Adverse Reactions with Undiluted, Bolus or Rapid Intravenous Administration [see Warnings and Precautions (5.1)]
- Pulmonary Embolism due to Pulmonary Vascular Precipitates [see Warnings and Precautions (5.2)]
- Hyperkalemia [see Warnings and Precautions (5.3)]
- Hyperphosphatemia and Hypocalcemia [see Warnings and Precautions (5.4)]
- Aluminum toxicity [see Warnings and Precautions (5.5)]
- Hypomagnesemia [see Warnings and Precautions (5.6)]
- Vein Damage and Thrombosis [see Warnings and Precautions (5.7)]

Manufactured by:

Lake Zurich, IL 60047
www.fresenius-kabi.com/us

451653A

PACKAGE LABEL

PACKAGE LABEL - PRINCIPAL DISPLAY – Potassium Phosphates Inj, USP 5 mL Vial Label

NDC 65219-052-09 860529

POTASSIUM

PHOSPHATES

INJECTION, USP

Phosphorus 15 mmol/5 mL

(3 mmol/mL)

Potassium 22 mEq/5 mL

(4.4 mEq/mL)

CAUTION: MUST BE DILUTED

For intravenous use only

5 mL Single-Dose Vial Rx only

Discard Unused Portion

PACKAGE LABEL

PACKAGE LABEL - PRINCIPAL DISPLAY – Potassium Phosphates Inj, USP 5 mL Tray Label

NDC 65219-052-29 860529

POTASSIUM

PHOSPHATES

INJECTION, USP

Phosphorus 15 mmol/5 mL

(3 mmol/mL)

Potassium 22 mEq/5 mL

(4.4 mEq/mL)

CAUTION: MUST BE DILUTED

For intravenous use only

25 x 5 mL

Single-Dose Vials Rx only

Discard Unused Portion

PACKAGE LABEL

PACKAGE LABEL - PRINCIPAL DISPLAY – Potassium Phosphates Inj, USP 15 mL Vial Label

NDC 65219-054-09 860539

POTASSIUM PHOSPHATES

INJECTION, USP

Phosphorus 45 mmol/15 mL

(3 mmol/mL)

Potassium 66 mEq/15 mL

(4.4 mEq/mL)

CAUTION: MUST BE DILUTED

For intravenous use only

15 mL Single-Dose Vial

Discard Unused Portion Rx only

PACKAGE LABEL

PACKAGE LABEL - PRINCIPAL DISPLAY – Potassium Phosphates Inj, USP 15 mL Tray Label

NDC 65219-054-29 860539

POTASSIUM PHOSPHATES

INJECTION, USP

Phosphorus 45 mmol/15 mL

(3 mmol/mL)

Potassium 66 mEq/15 mL

(4.4 mEq/mL)

CAUTION: MUST BE DILUTED

For intravenous use only

25 x 15 mL

Single-Dose Vials Rx only

Discard Unused Portion

PACKAGE LABEL

PACKAGE LABEL - PRINCIPAL DISPLAY – Potassium Phosphates Inj, USP 50 mL Vial Label

NDC 65219-056-09 860569

POTASSIUM

PHOSPHATES

INJECTION, USP

Phosphorus 150 mmol/50 mL

(3 mmol/mL)

Potassium 220 mEq/50 mL

(4.4 mEq/mL)

Pharmacy Bulk Package –

Not for Direct Infusion

CAUTION: MUST BE DILUTED

For intravenous use only

50 mL Rx only

Discard Unused Portion

PACKAGE LABEL

PACKAGE LABEL - PRINCIPAL DISPLAY – Potassium Phosphates Inj, USP 50 mL Tray Label

NDC 65219-056-29 860569

POTASSIUM

PHOSPHATES

INJECTION, USP

Phosphorus 150 mmol/50 mL

(3 mmol/mL)

Potassium 220 mEq/50 mL

(4.4 mEq/mL)

Pharmacy Bulk Package –

Not for Direct Infusion

CAUTION: MUST BE DILUTED

For intravenous use only

25 x 50 mL

Discard Unused Portion Rx only